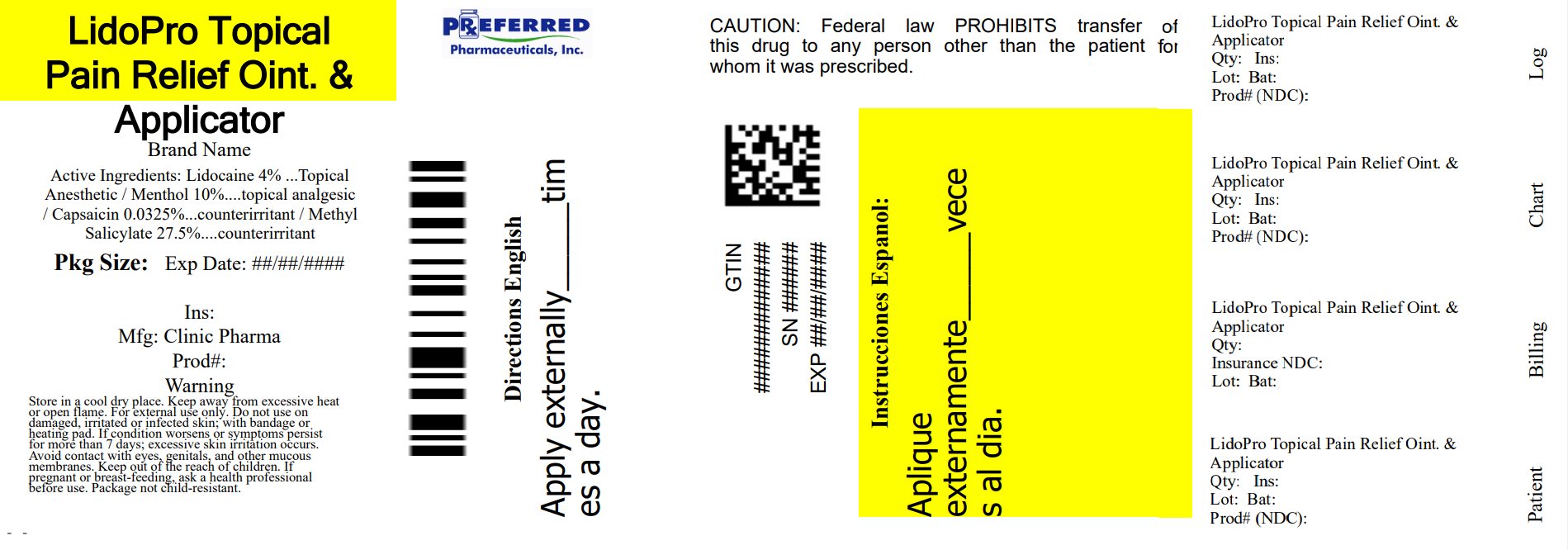 DRUG LABEL: LidoPro Pain Relief
NDC: 68788-8833 | Form: OINTMENT
Manufacturer: Preferred Pharmaceuticals Inc.
Category: otc | Type: HUMAN OTC DRUG LABEL
Date: 20250221

ACTIVE INGREDIENTS: MENTHOL, (+)- 10 mg/100 mg; LIDOCAINE HYDROCHLORIDE 4 mg/100 mg; METHYL SALICYLATE 27.5 mg/100 mg; CAPSAICIN 0.0325 mg/100 mg
INACTIVE INGREDIENTS: ALOE VERA LEAF; TROLAMINE; WATER; MATRICARIA CHAMOMILLA WHOLE; AMMONIUM ACRYLOYLDIMETHYLTAURATE/VP COPOLYMER; GLYCERYL MONOSTEARATE; PHENOXYETHANOL; CETYL ALCOHOL; DIMETHICONE, UNSPECIFIED; ETHYLHEXYLGLYCERIN; PEG-100 MONOSTEARATE; ALLANTOIN; EDETATE DISODIUM; GLYCERIN; INULIN LAURYL CARBAMATE; STEARIC ACID

83881-001 LidoPro Transdermal Pain Relief & Applicator

Active ingredient

- Capsicum annum fruit extract (capsaicin)
- Lidocaine HCL
- Menthol
- Methyl Salicylate

Purpose

- counterirritant
- anesthetic
- analgesic

Uses

For the temporary relief of joint pain and muscle pain associated with:

- arthritis
- simple backache
- muscle sprains
- muscle strains

Warnings

For external use only.

Do not use

- on damaged, irritated or infected skin
- with a bandage or heating pad
- if you are allergic to any ingredients in this product

When using this product

avoid contact with the eyes and mucous membranes

Stop use and ask doctor if

- condition worsens
- excessive skin
- irritation develops
- symptoms persist for more than 7 days
- symptoms clear up and occur again within 3 days

If pregnant or breast-feeding

ask a health professional before use.

Keep out of reach of children

If ingested, seek medical help or contact a Poison Control Center immediately.

Flammable

Keep away from excessive heat or open flame.

Directions

Adults and children 12 years of age and older:

- clean and dry the affected area
- apply product directly to skin, up to 4 times daily
- wash hands immediately after use

Children under 12 years of age: Consult physician.

Other information

- Store in a cool, dry place with lid tightly closed
- if the tamper-evident foil seal is not intact, do not use

Inactive ingredient

allantoin, aloe barbadensis leaf juice, ammonium acryloyldimethyltaurate/vp copolymer, cetyl alcohol, chamomilla recutita matricaria flower extract, dimethicone, disodium EDTA, ethylhexylglycerin, glycerin, glyceryl stearate, inulin lauryl carbamate, PEG-100 stearate, phenoxyethanol, stearic acid, triethanolamine, water

Questions?

(800) 224-2048 or info@clinicpharma.com

Relabeled By: Preferred Pharmaceuticals Inc.

NDC 68788-8833-9